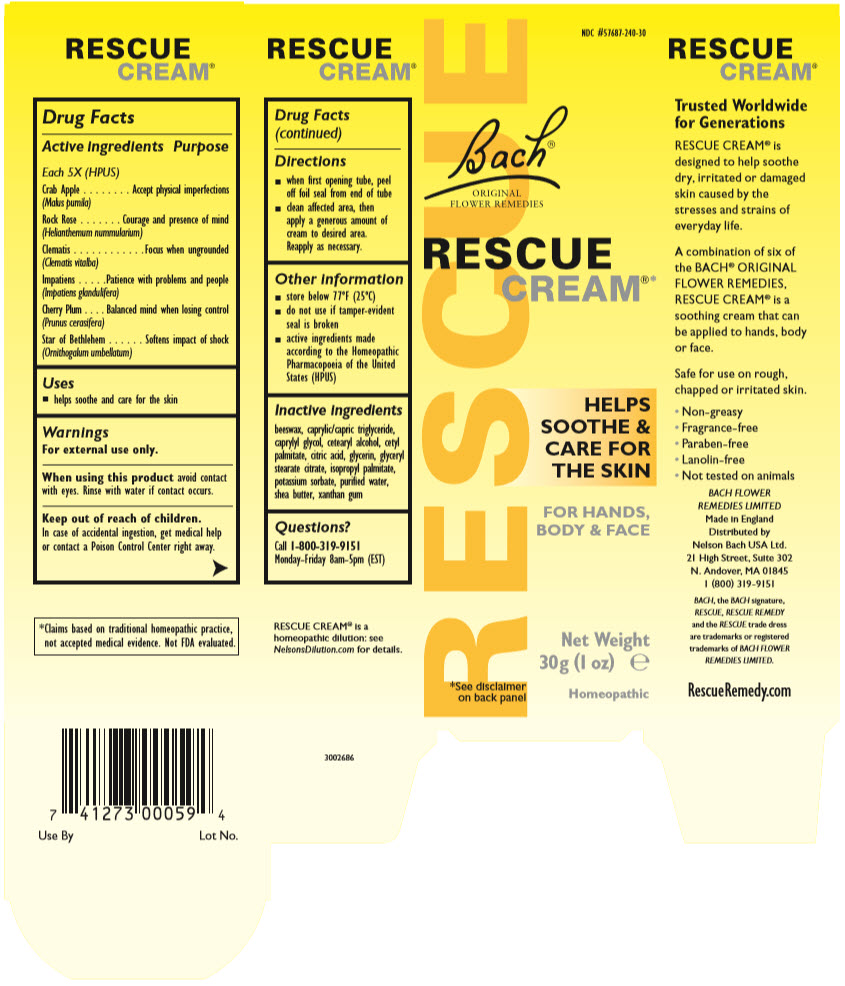 DRUG LABEL: Rescue
NDC: 57687-240 | Form: CREAM
Manufacturer: Nelson Bach USA, Ltd.
Category: homeopathic | Type: HUMAN OTC DRUG LABEL
Date: 20201102

ACTIVE INGREDIENTS: Helianthemum nummularium flower 5 [hp_X]/0.5 g; Clematis vitalba flower 5 [hp_X]/0.5 g; Impatiens glandulifera flower 5 [hp_X]/0.5 g; Prunus cerasifera flower 5 [hp_X]/0.5 g; Ornithogalum umbellatum Whole 5 [hp_X]/0.5 g; Malus domestica flower 5 [hp_X]/0.5 g
INACTIVE INGREDIENTS: Yellow Wax; Medium-Chain Triglycerides; caprylyl glycol; Cetostearyl Alcohol; Cetyl palmitate; Citric Acid Monohydrate; Glycerin; Glyceryl stearate citrate; Isopropyl palmitate; Potassium sorbate; water; Shea Butter; Xanthan gum

Rescue® Cream

Drug Facts

ACTIVE INGREDIENT

Active ingredients Each 5X (HPUS) | Purpose
Crab Apple (Malus pumila) | Accept physical imperfections
Rock Rose (Helianthemum nummularium) | Courage and presence of mind
Clematis (Clematis vitalba) | Focus when ungrounded
Impatiens (Impatiens glandulifera) | Patience with problems and people
Cherry Plum (Prunus cerasifera) | Balanced mind when losing control
Star of Bethlehem (Ornithogalum umbellatum) | Softens impact of shock

Uses

- helps soothe and care for the skin

Warnings

For external use only.

When using this product avoid contact with eyes. Rinse with water if contact occurs.

Keep out of reach of children.

In case of accidental ingestion, get medical help or contact a Poison Control Center right away.

Directions

- when first opening tube, peel off foil seal from end of tube
- clean affected area, then apply a generous amount of cream to desired area. Reapply as necessary.

Other information

- store below 77°F (25°C)
- do not use if tamper-evident seal is broken
- active ingredients made according to the Homeopathic Pharmacopoeia of the United States (HPUS)

Inactive ingredients

beeswax, caprylic/capric triglyceride, caprylyl glycol, cetearyl alcohol, cetyl palmitate, citric acid, glycerin, glyceryl stearate citrate, isopropyl palmitate, potassium sorbate, purified water, shea butter, xanthan gum

Questions?

Call 1-800-319-9151

Monday-Friday 8am-5pm (EST)

Distributed by
Nelson Bach USA Ltd.
21 High Street, Suite 302
N. Andover, MA 01845

PRINCIPAL DISPLAY PANEL - 30 g Tube Carton

RESCUE

NDC #57687-240-30

Bach®

ORIGINAL
FLOWER REMEDIES

RESCUE
CREAM®*

HELPS
SOOTHE &
CARE FOR
THE SKIN

FOR HANDS,
BODY & FACE

Net Weight
30g (1 oz) e

Homeopathic

*See disclaimer
on back panel